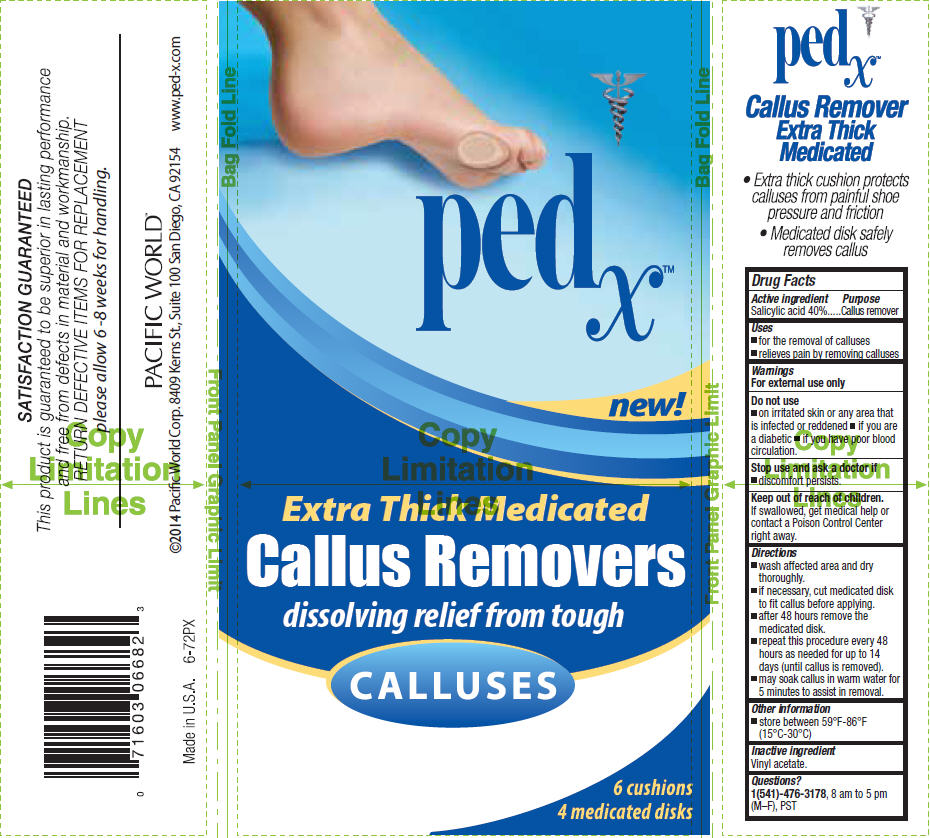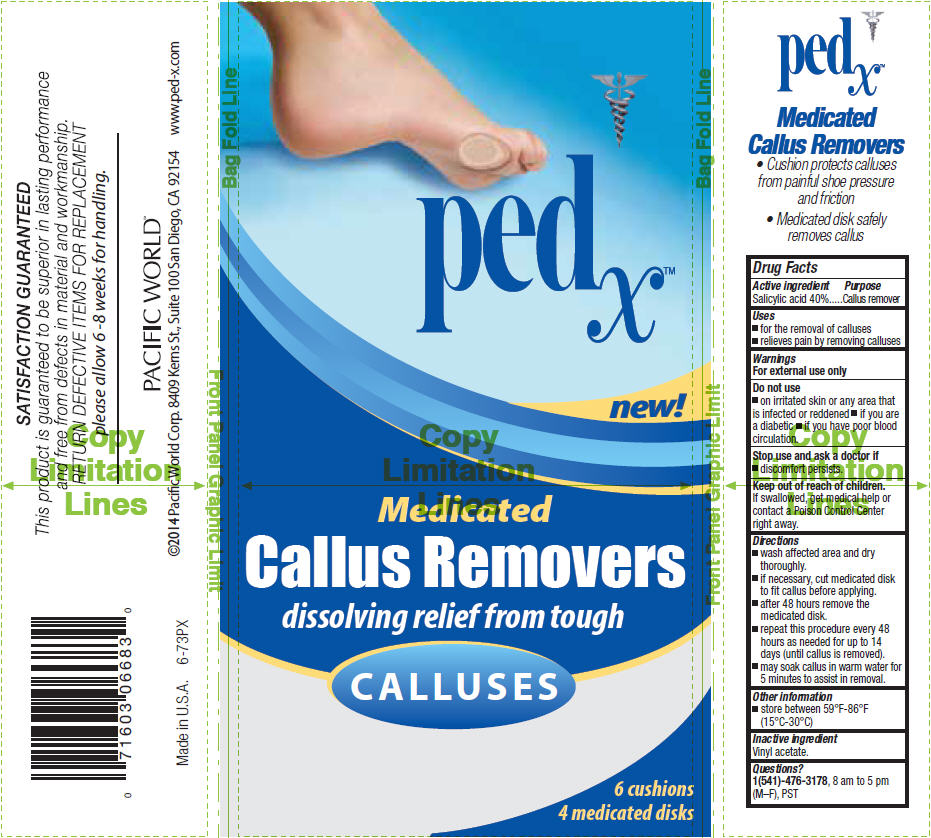 DRUG LABEL: Ped X Callus Removers, Extra Thick Medicated
NDC: 60193-401 | Form: PATCH
Manufacturer: Pacific World Corporation
Category: otc | Type: HUMAN OTC DRUG LABEL
Date: 20141017

ACTIVE INGREDIENTS: Salicylic acid 4 mg/1 1
INACTIVE INGREDIENTS: Vinyl acetate

Ped X™ Callus Removers

Drug Facts

Active ingredient

Salicylic acid 40%

Purpose

Callus remover

Uses

- for the removal of calluses
- relieves pain by removing calluses

Warnings

For external use only

Do not use

- on irritated skin or any area that is infected or reddened
- if you are a diabetic
- if you have poor blood circulation.

Stop use and ask a doctor if

- discomfort persists.

Keep out of reach of children. If swallowed, get medical help or contact a Poison Control Center right away.

Directions

- wash affected area and dry thoroughly.
- if necessary, cut medicated disk to fit callus before applying.
- after 48 hours remove the medicated disk.
- repeat this procedure every 48 hours as needed for up to 14 days (until callus is removed).
- may soak callus in warm water for 5 minutes to assist in removal.

Other information

- store between 59°F-86°F (15°C-30°C)

Inactive ingredient

Vinyl acetate.

Questions?

1(541)-476-3178, 8 am to 5 pm (M–F), PST

PRINCIPAL DISPLAY PANEL - 4 mg Patch Cello Pack - Extra Thick

pedx™

new!

Extra Thick Medicated

Callus Removers

dissolving relief from tough

CALLUSES

6 cushions
4 medicated disks

PRINCIPAL DISPLAY PANEL - 4 mg Patch Cello Pack - Medicated

pedx™

new!

Medicated

Callus Removers

dissolving relief from tough

CALLUSES

6 cushions
4 medicated disks